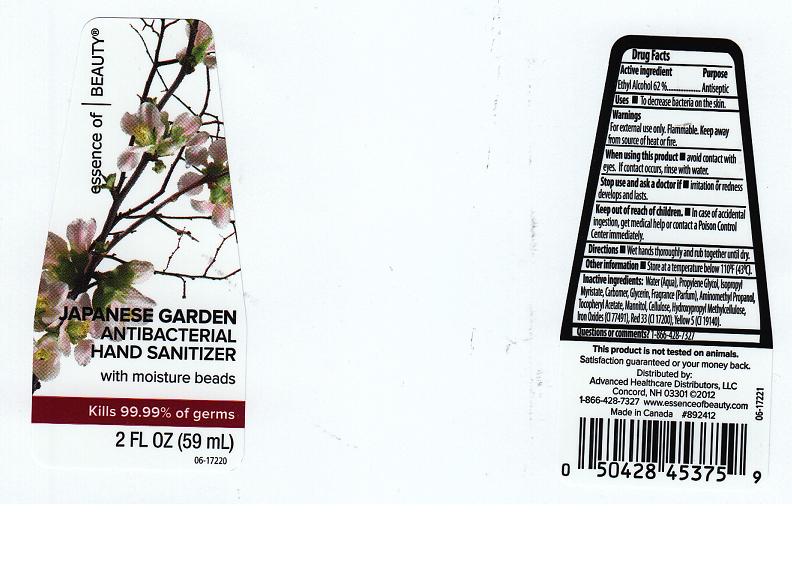 DRUG LABEL: ESSENCE OF BEAUTY
NDC: 59779-468 | Form: LIQUID
Manufacturer: CVS PHARMACY
Category: otc | Type: HUMAN OTC DRUG LABEL
Date: 20120612

ACTIVE INGREDIENTS: ALCOHOL 62 mL/100 mL
INACTIVE INGREDIENTS: WATER; PROPYLENE GLYCOL; ISOPROPYL MYRISTATE; CARBOMER 934; GLYCERIN; AMINOMETHYLPROPANOL; .ALPHA.-TOCOPHEROL ACETATE; MANNITOL; POWDERED CELLULOSE; HYPROMELLOSE 2208 (4000 MPA.S); FERRIC OXIDE RED; D&C RED NO. 33; FD&C YELLOW NO. 5

DRUG FACTS

ACTIVE INGREDIENT

ETHYL ALCOHOL 62%

PURPOSE

ANTISEPTIC

USES

TO DECREASE BACTERIA ON THE SKIN.

WARNINGS

FOR EXTERNAL USE ONLY. FLAMMABLE. KEEP AWAY FROM SOURCE OF HEAT OR FIRE.

WHEN USING THIS PRODUCT

AVOID CONTACT WITH EYES. IF CONTACT OCCURS, RINSE WITH WATER.

STOP USE AND ASK A DOCTOR IF

IRRITATION OR REDNESS DEVELOPS AND LASTS.

KEEP OUT OF REACH OF CHILDREN

IN CASE OF ACCIDENTAL INGESTION, GET MEDICAL HELP OR CONTACT A POISON CONTROL CENTER IMMEDIATELY.

DIRECTIONS

WET HANDS THOROUGHLY AND RUB TOGETHER UNTIL DRY.

OTHER INFORMATION

STORE AT A TEMPERATURE BELOW 110F (43C).

INACTIVE INGREDIENTS:

WATER (AQUA), PROPYLENE GLYCOL, ISOPROPYL MYRISTATE, CARBOMER, GLYCERIN, FRAGRANCE (PARFUM), AMINOMETHYL PROPANOL, TOCOPHERYL ACETATE, MANNITOL, CELLULOSE, HYDROXYPROPYL METHYLCELLULOSE, IRON OXIDES (CI 77491), RED 33 (CI 17200), YELLOW 5 (CI 19140).

QUESTIONS OR COMMENTS?

1-866-428-7327